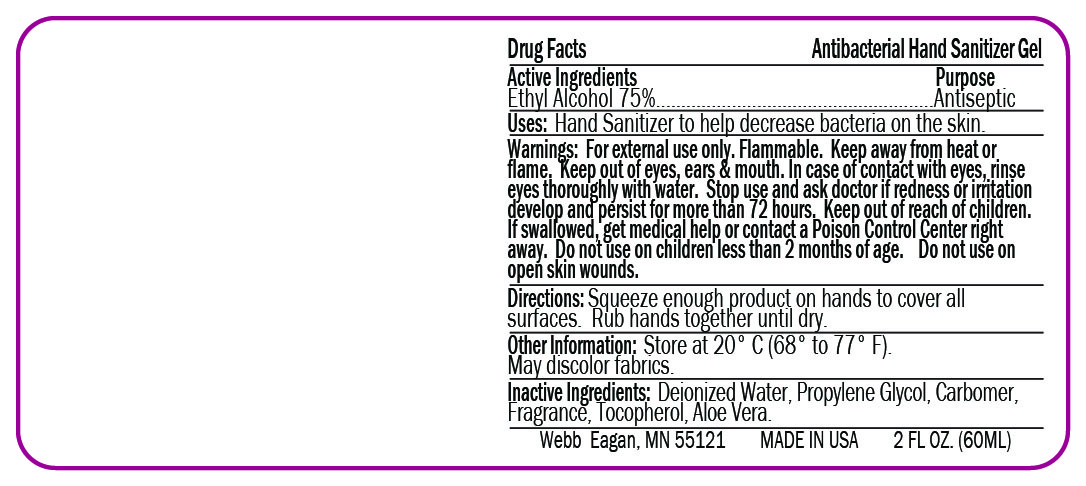 DRUG LABEL: Hand Sanitizer
NDC: 70445-414 | Form: GEL
Manufacturer: Webb Business Promotions, Inc
Category: otc | Type: HUMAN OTC DRUG LABEL
Date: 20220104

ACTIVE INGREDIENTS: ALCOHOL 75 mL/100 mL
INACTIVE INGREDIENTS: TOCOPHEROL; ALOE VERA LEAF; PROPYLENE GLYCOL 1 mL/100 mL; CARBOMER HOMOPOLYMER, UNSPECIFIED TYPE 1 mL/100 mL; WATER

Anti-Bacterial Hand Sanitizer Gel

This is a hand sanitizer manufactured according to the Temporary Policy for Preparation of Certain Alcohol-Based Hand Sanitizer Products During the Public Health Emergency (CoViD-19); Guidance for Industry.

The hand sanitizer is manufactured using only the following United States Pharmacopoeia (USP) grade ingredients in the preparation of the product (percentage in final product formulation) consistent with World Health Organization (WHO) recommendations:

1. Alcohol (ethanol) (USP or Food Chemical Codex (FCC) grade) (75%, volume/volume (v/v)) in an aqueous solution denatured according to Alcohol and Tobacco Tax and Trade Bureau regulations in 27 CFR part 20

Active Ingredient(s)

Alcohol 75% v/v. Purpose: Antiseptic

Purpose

Antiseptic, Hand Sanitizer

Use

Hand Sanitizer to help decrese bacteria on the skin.

Warnings

For external use only. Flammable. Keep away from heat or flame

Do not use

- in children less than 2 months of age
- on open skin wounds

When using this product keep out of eyes, ears, and mouth. In case of contact with eyes, rinse eyes thoroughly with water.
Stop use and ask a doctor if irritation or rash occurs. These may be signs of a serious condition.
Keep out of reach of children. If swallowed, get medical help or contact a Poison Control Center right away.

Stop use and ask a doctor if irritation or rash occurs.

Keep out of reach of children. If swallowed, get medical help or contact a Poison Control Center right away.

Directions

- Squeeze enough product on hands to cover all surfaces. Rub hands together until dry.

Other information

- Store between 20C (68-77F)
- May discolore fabrics

Inactive ingredients

Water, Propylene Glycol, Carbomer, Tocopherol, Aloe Vera

Package Label - Principal Display Panel

240 mL NDC: 70445-414-18